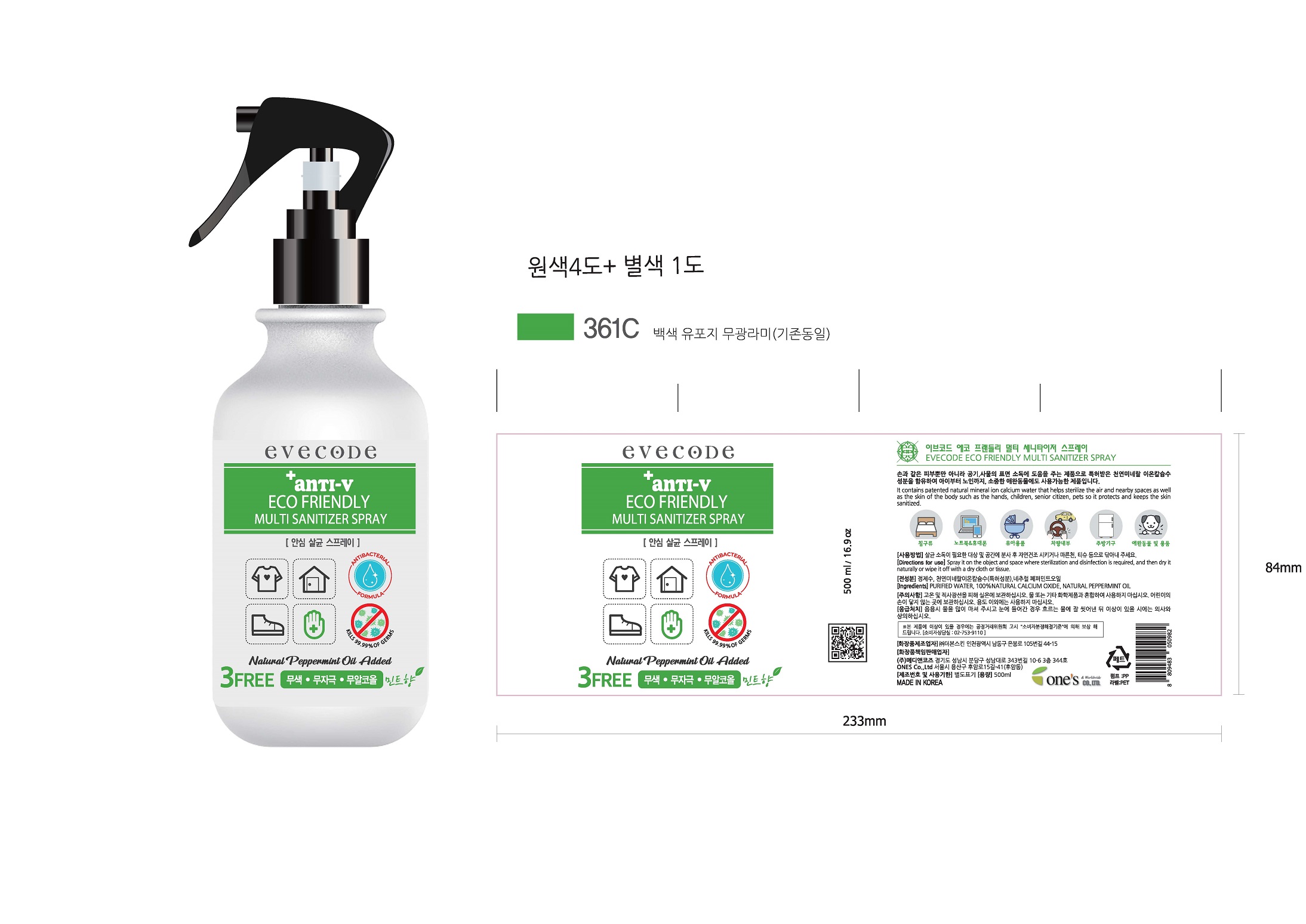 DRUG LABEL: EVECODE ECO FRIENDLY MULTI SANITIZERspray
NDC: 73772-0002 | Form: LIQUID
Manufacturer: MEDINCOZ INC.
Category: otc | Type: HUMAN OTC DRUG LABEL
Date: 20200501

ACTIVE INGREDIENTS: LIME (CALCIUM OXIDE) 20 g/100 mL
INACTIVE INGREDIENTS: WATER

Drug Facts

ACTIVE INGREDIENT

calcium oxide

INACTIVE INGREDIENT

water, peppermint oil

PURPOSE

helps sterilize the air and nearby spaces as well as the skin of the body such as the hands, children, serion citizen, pets

KEEP OUT OF REACH OF THE CHILDREN

INDICATIONS AND USAGE

Spray it on the object and space where sterilization and disinfection is required, and then dry it naturally or wipe it off with a dry cloth or tissue.

WARNINGS

For external use only.

Flammable, keep away from fire or flame.

Store at room temperature, away from high temperatures and direct sunlight. Do not mix with water or other chemicals. Keep this product out of the reach of children. Please do not use for other purposes.

Emergency treatment : In case of accidental drinking, drink plenty of water. If it gets into your eyes, wash with running water and consult a doctor if there is any problem.

DOSAGE AND ADMINISTRATION

Spray it on the hands and object and space where sterilization and disinfection is required, and then dry it naturally or wipe it off with a dry cloth or tissue.